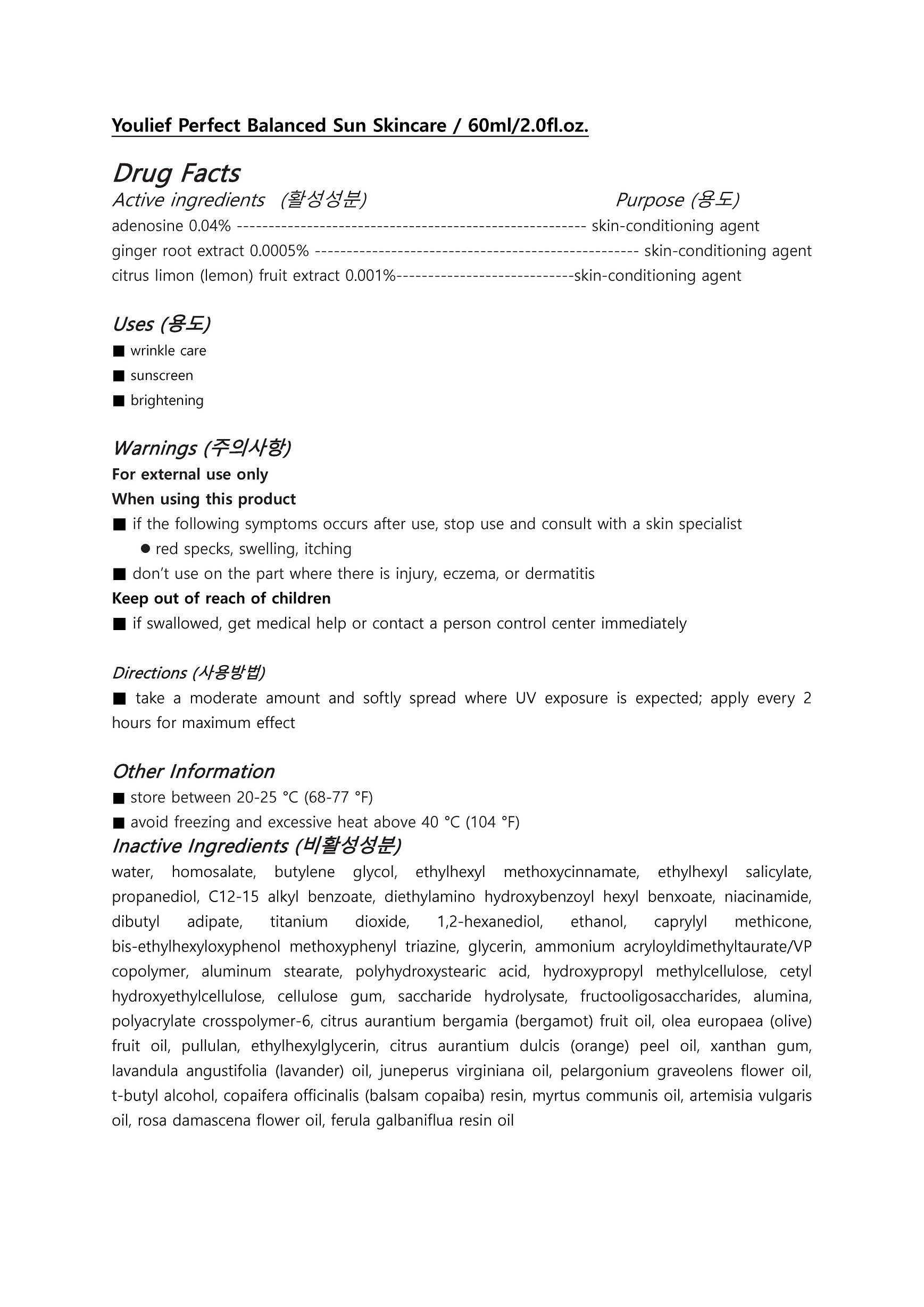 DRUG LABEL: Youllief Perfect Balanced Sun Skincare
NDC: 73560-0004 | Form: CREAM
Manufacturer: Plcoskin
Category: otc | Type: HUMAN OTC DRUG LABEL
Date: 20200127

ACTIVE INGREDIENTS: CITRUS LIMON FRUIT OIL 0.001 g/100 mL; ADENOSINE 0.04 g/100 mL; GINGER 0.0005 g/100 mL
INACTIVE INGREDIENTS: WATER; BUTYLENE GLYCOL

Drug Facts

ACTIVE INGREDIENT

Adenosine, ginger root extract, citrus limon (lemon) fruit extract

INACTIVE INGREDIENT

water, homosalate, butylene glycol, ethylhexyl methoxycinnamate, ethylhexyl salicylate, propanediol, C12-15 alkyl benzoate, diethylamino hydroxybenzoyl hexyl benxoate, niacinamide, dibutyl adipate, titanium dioxide, 1,2-hexanediol, ethanol, caprylyl methicone, bis-ethylhexyloxyphenol methoxyphenyl triazine, glycerin, ammonium acryloyldimethyltaurate/VP copolymer, aluminum stearate, polyhydroxystearic acid, hydroxypropyl methylcellulose, cetyl hydroxyethylcellulose, cellulose gum, saccharide hydrolysate, fructooligosaccharides, alumina, polyacrylate crosspolymer-6, citrus aurantium bergamia (bergamot) fruit oil, olea europaea (olive) fruit oil, pullulan, ethylhexylglycerin, citrus aurantium dulcis (orange) peel oil, xanthan gum, lavandula angustifolia (lavander) oil, juneperus virginiana oil, pelargonium graveolens flower oil, t-butyl alcohol, copaifera officinalis (balsam copaiba) resin, myrtus communis oil, artemisia vulgaris oil, rosa damascena flower oil, ferula galbaniflua resin oil

PURPOSE

■ wrinkle care

■ sunscreen

■ brightening

keep out of reach of the children

INDICATIONS AND USAGE

Every morning and evening, after the usage of ampoules or essences, take a moderate amount of the cosmetics and softly spread along the eye area and parts where wrinkles are considerates then gently pat for the skin to absorb.

WARNINGS

For external use only
When using this product

■ if the following symptoms occurs after use, stop use and consult with a skin specialist

red specks, swelling, itching

■ don’t use on the part where there is injury, eczema, or dermatitis

Keep out of reach of children

■ if swallowed, get medical help or contact a person control center immediately

DOSAGE AND ADMINISTRATION

for external use only